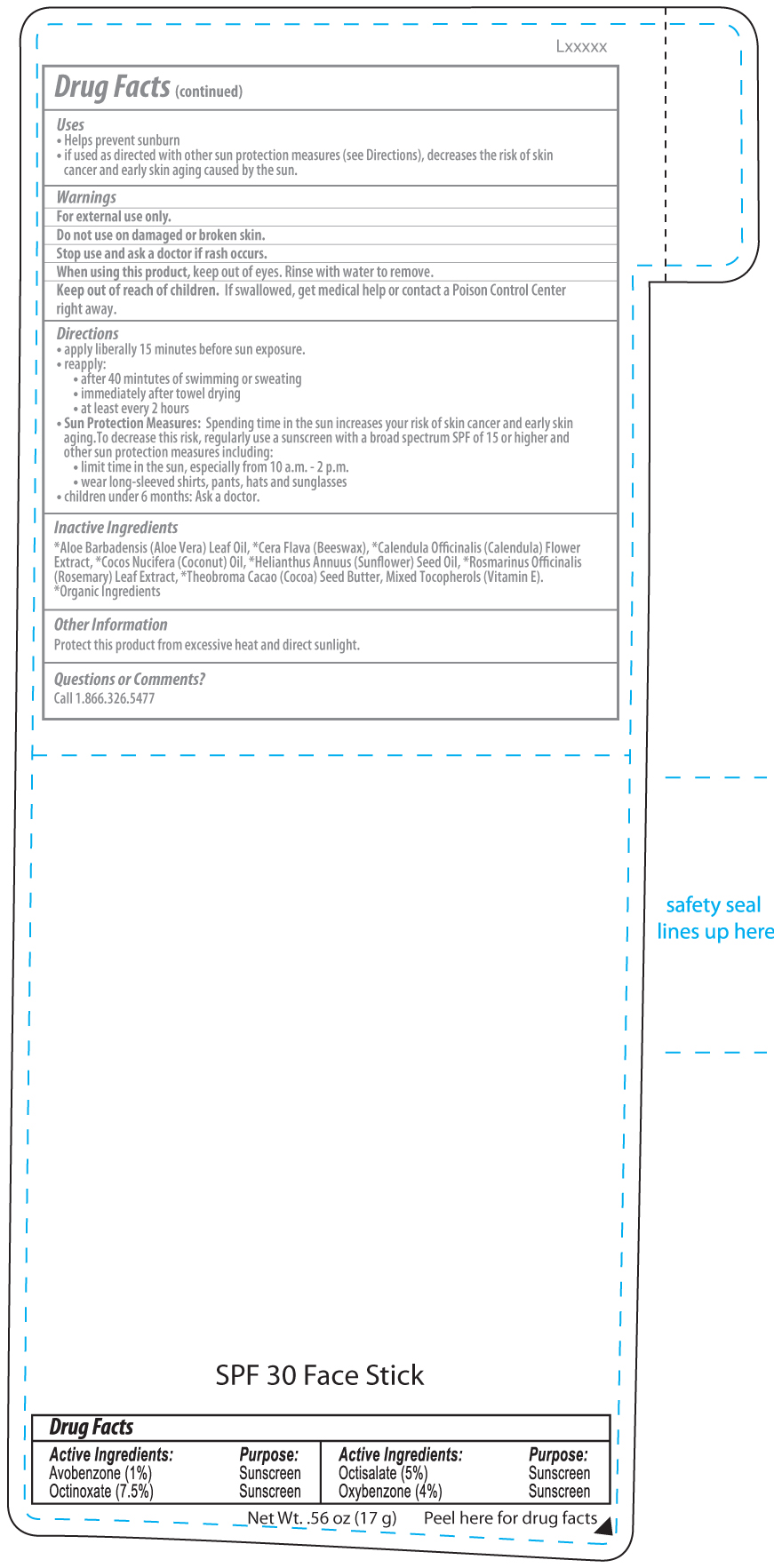 DRUG LABEL: Eco SPF30 Sun Stick
NDC: 58418-274 | Form: STICK
Manufacturer: Tropical Enterprises International, Inc
Category: otc | Type: HUMAN OTC DRUG LABEL
Date: 20200203

ACTIVE INGREDIENTS: OCTISALATE 5 mg/1 mL; OXYBENZONE 4 mg/1 mL; OCTINOXATE 7.5 mg/1 mL; AVOBENZONE 1 mg/1 mL
INACTIVE INGREDIENTS: ALOE VERA LEAF; ROSMARINUS OFFICINALIS FLOWERING TOP OIL; SUNFLOWER OIL; CALENDULA OFFICINALIS FLOWER; COCONUT OIL; APIS CERANA WORKER SECRETION; COCOA BUTTER; TOCOPHEROL

Broad Spectrum Spf30 Sunstick - EL x274

ACTIVE INGREDIENT

Avobenzone (1%)

Octinoxate (7.5%)

Octisalate (5%)

Oxybenzone (4%)

Uses

- Helps prevent sunburn
- If used as directed with other sun protection measures (see Cirections), decreases the risk of skin cancer and early skin aging caused by the sun.

Warnings

For external use only.

Do not use on damaged or broken skin.

Stop use and ask a doctor if rash occurs.

When using this product, keep out of eyes. Rinse with water to remove.

Keep out of reach of children. If swallowed, get medical help or contact a Poison Control Center right away.

Directions

- apply liberally 15 minutes before sun exposure.
- reapply:
  - after 40 minutes of swimming or sweating
  - immediately after towel drying
  - at least every 2 hours
  - Sun Protection Measures: Spending time in the sun increases your risk of skin cancer and early skin aging. To decrease this risk, regularly use a sunscreen with a broad spectrum SPF of 15 or higher and other sun protection measures including:
  - limit time in the sun, especially from 10 a.m. - 2 p.m.
  - wear long-sleeved shirts; pants, hats and sunglasses
  - children under 6 months: Ask a doctor.

Inactive Ingredients

*Aloe Barbadenis (Aloe Vera) Leaf Oil, *Cera Flava (Beeswax), *Calendula Officinalis (Calendula) Flower Extract, *Cocos Nucifera (Cocounut) Oil, "Hellanthus Annuus (Sunflower) Seed Oil, *Rosmarinus Officinalis (Rosemary) Leaf Extract, *Theeobroma Cacao (Cocoa) Seed Butter, Mixed Tocopherols (Vitamin E).

*Organic Ingredients

Other Information

Protect this product from excessive heat and direct sunlight.

Questions or Comments?

Call 1.866.326.5477